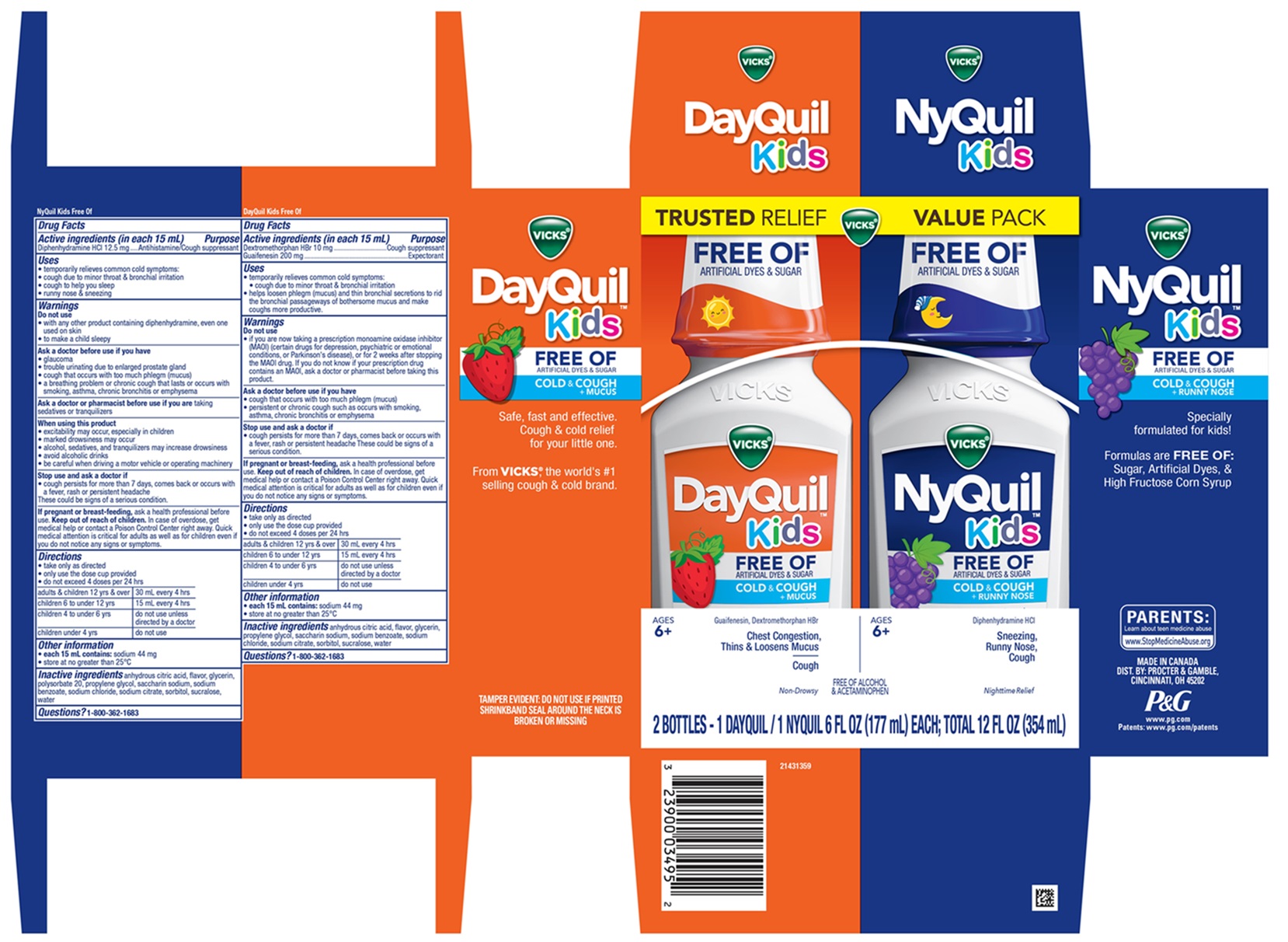 DRUG LABEL: Vicks DayQuil Kids and Vicks NyQuil Kids
NDC: 84126-312 | Form: KIT | Route: ORAL
Manufacturer: The Procter & Gamble Manufacturing Company
Category: otc | Type: HUMAN OTC DRUG LABEL
Date: 20251201

ACTIVE INGREDIENTS: GUAIFENESIN 200 mg/15 mL; DEXTROMETHORPHAN HYDROBROMIDE 10 mg/15 mL; DIPHENHYDRAMINE HYDROCHLORIDE 12.5 mg/15 mL
INACTIVE INGREDIENTS: SODIUM CHLORIDE; GLYCERIN; SODIUM BENZOATE; SORBITOL; ANHYDROUS CITRIC ACID; PROPYLENE GLYCOL; WATER; SACCHARIN SODIUM; SODIUM CITRATE; SUCRALOSE; SODIUM BENZOATE; ANHYDROUS CITRIC ACID; WATER; SACCHARIN SODIUM; SODIUM CITRATE; GLYCERIN; SORBITOL; SUCRALOSE; POLYSORBATE 20; PROPYLENE GLYCOL; SODIUM CHLORIDE

Vicks® DayQuil™ Kids / Vicks® NyQuil™ Kids FREE OF ARTIFICIAL DYES & SUGAR
COLD & COUGH + Convenience Pack

Vicks® DayQuil™ Kids FREE OF ARTIFICIAL DYES & SUGAR COLD & COUGH + MUCUS, Liquid

Drug Facts

Active ingredients (in each 15 mL)

Dextromethorphan HBr 10 mg
Guaifenesin 200 mg

Purpose

Cough suppressant
Expectorant

Uses

- temporarily relieves common cold symptoms:
- cough due to minor throat & bronchial irritation
- helps loosen phlegm (mucus) and thin bronchial secretions to rid the bronchial passageways of bothersome mucus and make coughs more productive.

Do not use

- if you are now taking a prescription monoamine oxidase inhibitor (MAOI) (certain drugs for depression, psychiatric or emotional conditions, or Parkinson's disease), or for 2 weeks after stopping the MAOI drug. If you do not know if your prescription drug contains an MAOI, ask a doctor or pharmacist before taking this product.

Ask a doctor before use if you have

- cough that occurs with too much phlegm (mucus)
- persistent or chronic cough such as occurs with smoking, asthma, chronic bronchitis or emphysema

Stop use and ask a doctor if

- cough persists for more than 7 days, comes back or occurs with a fever, rash or persistent headache

These could be signs of a serious condition.

If pregnant or breast-feeding,

ask a health professional before use.

Keep out of reach of children.

OVERDOSAGE

In case of overdose, get medical help or contact a Poison Control Center right away. Quick medical attention is critical for adults as well as for children even if you do not notice any signs or symptoms.

Directions

- take only as directed
- only use the dose cup provided
- do not exceed 4 doses per 24 hrs

adults & children 12 yrs & over | 30 mL every 4 hrs
children 6 to under 12 yrs | 15 mL every 4 hrs
children 4 to under 6 yrs | do not use unless directed by a doctor
children under 4 yrs | do not use

Other information

- each 15 mL contains:sodium 44 mg
- store at no greater than 25°C

Inactive ingredients

anhydrous citric acid, flavor, glycerin, propylene glycol, saccharin sodium, sodium benzoate, sodium chloride, sodium citrate, sorbitol, sucralose, water

Questions?

1-800-362-1683

TAMPER EVIDENT: DO NOT USE IF PRINTED SHRINKBAND SEAL AROUND THE NECK IS BROKEN OR MISSING

MADE IN CANADA

DIST. BY: PROCTER & GAMBLE, CINCINNATI, OH 45202

Vicks ®NyQuil™ Kids FREE OF ARTIFICIAL DYES & SUGAR COLD & COUGH + RUNNY NOSE, Liquid

Drug Facts

Active ingredients (in each 15 mL)

Diphenhydramine HCl 12.5 mg

Purpose

Antihistamine/Cough suppressant

Uses

- temporarily relieves common cold symptoms:
- cough due to minor throat & bronchial irritation
- cough to help you sleep
- runny nose & sneezing

Do not use

- with any other product containing diphenhydramine, even one used on skin
- to make a child sleepy

Ask a doctor before use if you have

- glaucoma
- trouble urinating due to enlarged prostate gland
- cough that occurs with too much phlegm (mucus)
- a breathing problem or chronic cough that lasts or occurs with smoking, asthma, chronic bronchitis or emphysema

Ask a doctor or pharmacist before use if you are

taking sedatives or tranquilizers

When using this product

- excitability may occur, especially in children
- marked drowsiness may occur
- alcohol, sedatives, and tranquilizers may increase drowsiness
- avoid alcoholic drinks
- be careful when driving a motor vehicle or operating machinery

Stop use and ask a doctor if

- cough persists for more than 7 days, comes back or occurs with a fever, rash or persistent headache

These could be signs of a serious condition.

If pregnant or breast-feeding,

ask a health professional before use.

Keep out of reach of children.

OVERDOSAGE

In case of overdose, get medical help or contact a Poison Control Center right away. Quick medical attention is critical for adults as well as for children even if you do not notice any signs or symptoms.

Directions

- take only as directed
- only use the dose cup provided
- do not exceed 4 doses per 24 hrs

adults & children 12 yrs & over | 30 mL every 4 hrs
children 6 to under 12 yrs | 15 mL every 4 hrs
children 4 to under 6 yrs | do not use unless directed by a doctor
children under 4 yrs | do not use

Other information

- each 15 mL contains:sodium 44 mg
- store at no greater than 25°C

Inactive ingredients

anhydrous citric acid, flavor, glycerin, polysorbate 20, propylene glycol, saccharin sodium, sodium benzoate, sodium chloride, sodium citrate, sorbitol, sucralose, water

Questions?

1-800-362-1683

TAMPER EVIDENT: DO NOT USE IF PRINTED SHRINKBAND SEAL AROUND THE NECK IS BROKEN OR MISSING

MADE IN CANADA

DIST. BY: PROCTER & GAMBLE

CINCINNATI, OH 45202

PRINCIPAL DISPLAY PANEL - Convenience Pack

Vicks® DayQuil™ Kids FREE OF ARTIFICIAL DYES & SUGAR / Vicks® NyQuil™ Kids FREE OF ARTIFICIAL DYES & SUGAR
COLD & COUGH + Convenience Pack

TRUSTEDRELIEF

VICKS®

VALUEPACK

Vicks® DayQuil™ Kids FREE OF ARTIFICIAL DYES & SUGAR

COLD & COUGH + MUCUS

Guaifenesin, Dextromethorphan HBr

Chest Congestion,

Thins & Loosens Mucus

Cough

Non-Drowsy

Ages 6+

FREE OF ALCOHOL & ACETAMINOPHEN

Vicks®NyQuil™ Kids FREE OF ARTIFICIAL DYES & SUGAR

COLD & COUGH + RUNNY NOSE

Diphenhydramine HCl

Sneezing,

Runny Nose,

Cough Nighttime Relief

Ages 6+

FREE OF ALCOHOL & ACETAMINOPHEN

2 BOTTLES - 1 DAYQUIL/1NYQUIL 6 FL OZ (177 mL) EACH; TOTAL 12 FL OZ (354 mL)